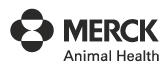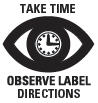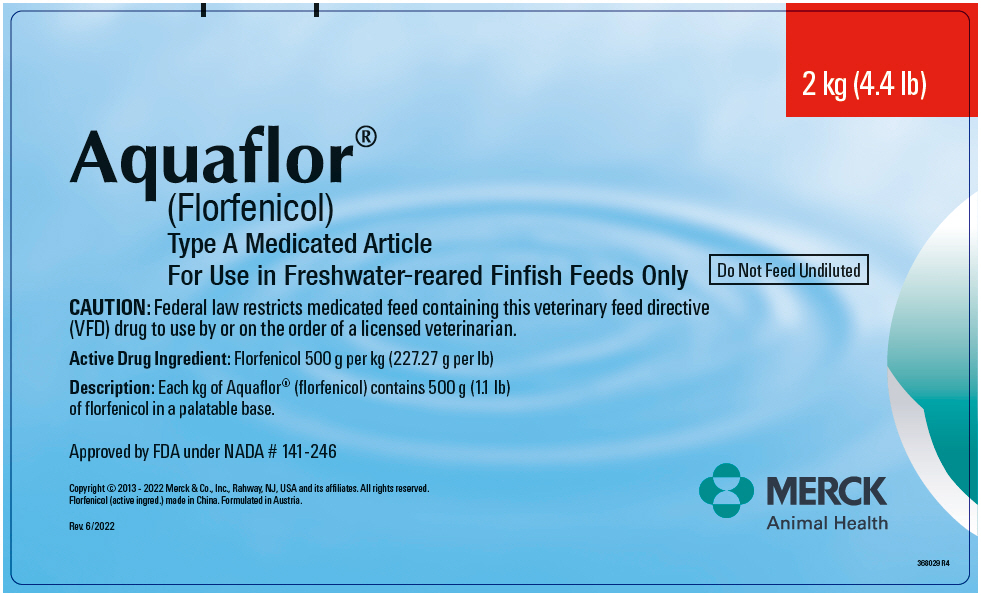 DRUG LABEL: Aquaflor
NDC: 0061-1355 | Form: POWDER
Manufacturer: Merck Sharp & Dohme Corp.
Category: animal | Type: VFD TYPE A MEDICATED ARTICLE ANIMAL DRUG LABEL
Date: 20250925

ACTIVE INGREDIENTS: FLORFENICOL 500 g/1 kg

Aquaflor®
(Florfenicol)

Type A Medicated Article
For Use in Freshwater-reared Finfish Feeds Only

Do Not Feed Undiluted

CAUTION

Federal law restricts medicated feed containing this veterinary feed directive (VFD) drug to use by or on the order of a licensed veterinarian.

Active Drug Ingredient

Florfenicol 500 g per kg (227.27 g per lb)

Inert ingredients

Lactose and Povidone.

Description

Each kg of Aquaflor® (florfenicol) contains 500 g (1.1 lb) of florfenicol in a palatable base.

Indications

Fish Species | Indication | Florfenicol (mg/kg body weight/day) | Florfenicol (grams/ton)
Freshwater-reared salmonids | For the control of mortality due to furunculosis associated with Aeromonas salmonicida. | 10 - 15 | 182-2,724
Freshwater-reared salmonids | For the control of mortality due to coldwater disease associated with Flavobacterium psychrophilum. | 10 - 15 | 182-2,724
Freshwater-reared finfish | For the control of mortality due to columnaris disease associated with Flavobacterium columnare. | 10 - 15 | 182-2,724
Catfish | For the control of mortality due to enteric septicemia of catfish associated with Edwardsiella ictaluri. | 10 - 15 | 182-2,724
Freshwater-reared warmwater finfish | For the control of mortality due to streptococcal septicemia associated with Streptococcus iniae. | 15 | 273- 2,724
Caution: Not for use in animals intended for breeding purposes. The effects of florfenicol on reproductive performance have not been determined. Toxicity studies in dogs, rats, and mice have associated the use of florfenicol with testicular degeneration and atrophy. For catfish, a dose related decrease in hematopoietic/lymphopoietic tissue may occur. The time required for the hematopoietic/lymphopoietic tissues to regenerate was not evaluated.

RESIDUE WARNING

Feeds containing Aquaflor® (florfenicol) must be withdrawn 15 days prior to slaughter.

IMPORTANT

This product has been evaluated in salmonid and catfish feeds and should be used in feeds nutritionally similar to these evaluated feeds. Refer to the Freedom of Information Summary for details. Must be thoroughly mixed in feeds or surface-coated (top-coated) onto the feeds before use.

Mixing Instructions

For incorporation into feed pellets: For making Aquaflor® (florfenicol) Type C Medicated Feed:

a) Aquaflor® (florfenicol) is added to other feed ingredients in the mixer prior to extrusion,
b) the ingredients are mixed thoroughly to insure homogeneity,
c) the mixture is steam pelleted or extruded and pellets are dried,
d) medicated feed pellets are mixed/coated with a predetermined amount of fish or vegetable oil, and
e) at the completion of mixing, the product is transferred to a storage tank for packaging or transport.

For surface-coating (top-coating) onto feed pellets: There are two methods for making Aquaflor® (florfenicol) Type C Medicated Feed by top-coating.

Method 1:

a) add a known quantity of fish feed into a mixer,
b) weigh out Aquaflor® (florfenicol),
c) mix Aquaflor® with feed pellets,
d) medicated feed pellets are mixed/coated with a predetermined amount of fish or vegetable oil, and
e) at the completion of mixing, the product is transferred to a storage tank for packaging or transport.

Method 2:

a) weigh out fish oil or vegetable oil into a bucket,
b) weigh out Aquaflor® (florfenicol) and mix thoroughly with the oil in the bucket,
c) add a known quantity of fish feed into a mixer,
d) add the Aquaflor® (florfenicol) and oil mixture to the feed in the mixer, slowly, while the mixer is running at low speed,
e) at the completion of mixing, the product is transferred to a storage tank for packaging or transport.

Example of Aquaflor® (florfenicol) Inclusion Rates for Preparation of Type C Medicated Feed
Feeding Rate | Florfenicol Concentration in Feed |  | Amount of Aquaflor® (florfenicol) per Ton of Feed |  | Biomass of Fish Medicated per Ton of Feed per 10-day Treatment Period
% Biomass | Grams/ton |  | lbs |  | lbs
 | Dose 10 mg/kg | Dose 15 mg/kg | Dose 10 mg/kg | Dose 15 mg/kg
0.5 | 1,816 | 2,724 | 8 | 12 | 40,000
1 | 908 | 1,362 | 4 | 6 | 20,000
2 | 454 | 681 | 2 | 3 | 10,000
3 | 300 | 450 | 1.32 | 1.98 | 6,666
5 | 182 | 273 | 0.8 | 1.2 | 4,000

Feeding Directions

Feed as the sole ration for 10 consecutive days. Aquaflor® (florfenicol) medicated feed should only be administered once disease has been appropriately diagnosed. Feeding fish at a percent of biomass and corresponding florfenicol concentration included in the table above will deliver the appropriate florfenicol dose.

Caution

Feed containing Aquaflor® (florfenicol) shall not be fed to finfish for more than 10 days. Following administration, fish should be re-evaluated by a licensed veterinarian before initiating a further course of therapy. The expiration date for VFD for Aquaflor® (florfenicol) must not exceed 6 months from the date of issuance. VFD for Aquaflor® (florfenicol) shall not be refilled.

Sunburn, skin lesions, and skin sloughing have been reported in salmonids treated with florfenicol. Not all adverse drug events are reported to FDA CVM. It is not always possible to reliably estimate the adverse event incidence or to establish a causal relationship to product exposure using this data alone.

Before using this drug for the first time, you must inform the appropriate National Pollutant Discharge Elimination System (NPDES) permitting authority of your intentions and of the following information. Acute and chronic water quality benchmarks for the protection of freshwater aquatic life have been derived by FDA for florfenicol following EPA guidance for calculating Tier II water quality criteria for the Great Lakes System (40 CFR 132, App. A). The acute benchmark value (Secondary Maximum Concentration) is 20.6 mg/L (equivalent to one-half of the Secondary Acute Value). The chronic benchmark value (Secondary Continuous Concentration) is 0.23 mg/L (equivalent to the Final Plant Value). The NPDES authority may require an NPDES permit before you can discharge Aquaflor®. The water quality benchmark concentrations are not discharge limits, but may be used by the NPDES authority to derive such limits for the permit. Additional environmental information on Aquaflor® and the benchmark values are available in an environmental assessment posted at https://animaldrugsatfda.fda.gov/adafda/views/#/environmentalAssessments

WARNING

Avoid inhalation, oral exposure, and direct contact with skin or eyes. Operators mixing and handling Aquaflor® (florfenicol) should use protective clothing, gloves, goggles and NIOSH-approved dust mask. Wash thoroughly with soap and water after handling. If accidental eye contact occurs, immediately rinse thoroughly with water. If irritation persists, seek medical attention. Not for human consumption. Keep out of reach of children. The Safety Data Sheet (SDS) contains more detailed occupational safety information. For more information or to report adverse effects, call 1-800-224-5318. For customer service, call 1-800-521-5767. For a copy of SDS sheet, call 1-800-770-8878.

STORAGE CONDITIONS

Store at temperatures up to 25°C with excursions permitted to 40°C.

Approved by FDA under NADA # 141-246
Copyright © 2013 - 2022 Merck & Co., Inc., Rahway, NJ, USA and its affiliates. All rights reserved.
Formulated in Austria.
Rev. 6/2022

LOT:
EXP:

354296 R4

PRINCIPAL DISPLAY PANEL - 2 kg Pouch Label

2 kg (4.4 lb)

Aquaflor®
(Florfenicol)
Type A Medicated Article
For Use in Freshwater-reared Finfish Feeds Only

Do Not Feed Undiluted

CAUTION: Federal law restricts medicated feed containing this veterinary feed directive
(VFD) drug to use by or on the order of a licensed veterinarian.

Active Drug Ingredient: Florfenicol 500 g per kg (227.27 g per lb)

Description: Each kg of Aquaflor® (florfenicol) contains 500 g (1.1 lb)
of florfenicol in a palatable base.

Approved by FDA under NADA # 141-246

Copyright © 2013 - 2022 Merck & Co., Inc., Rahway, NJ, USA and its affiliates. All rights reserved.
Florfenicol (active ingred.) made in China. Formulated in Austria.

Rev. 6/2022

MERCK
Animal Health

368029 R4